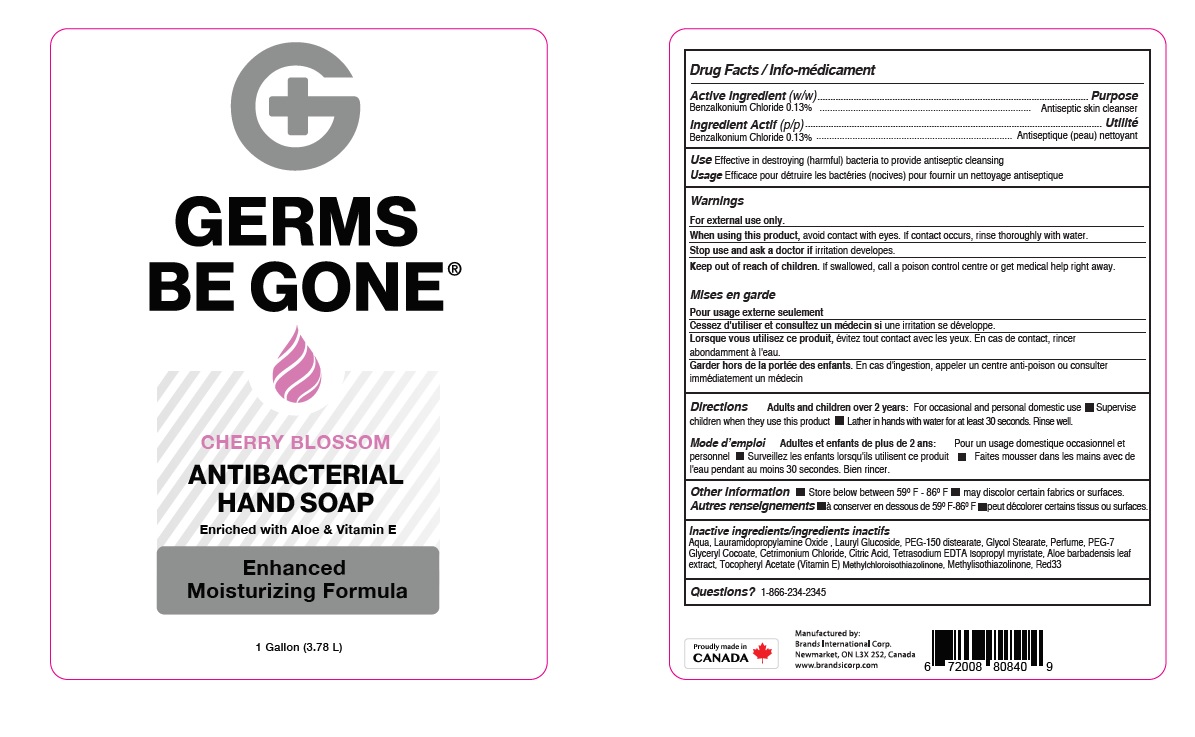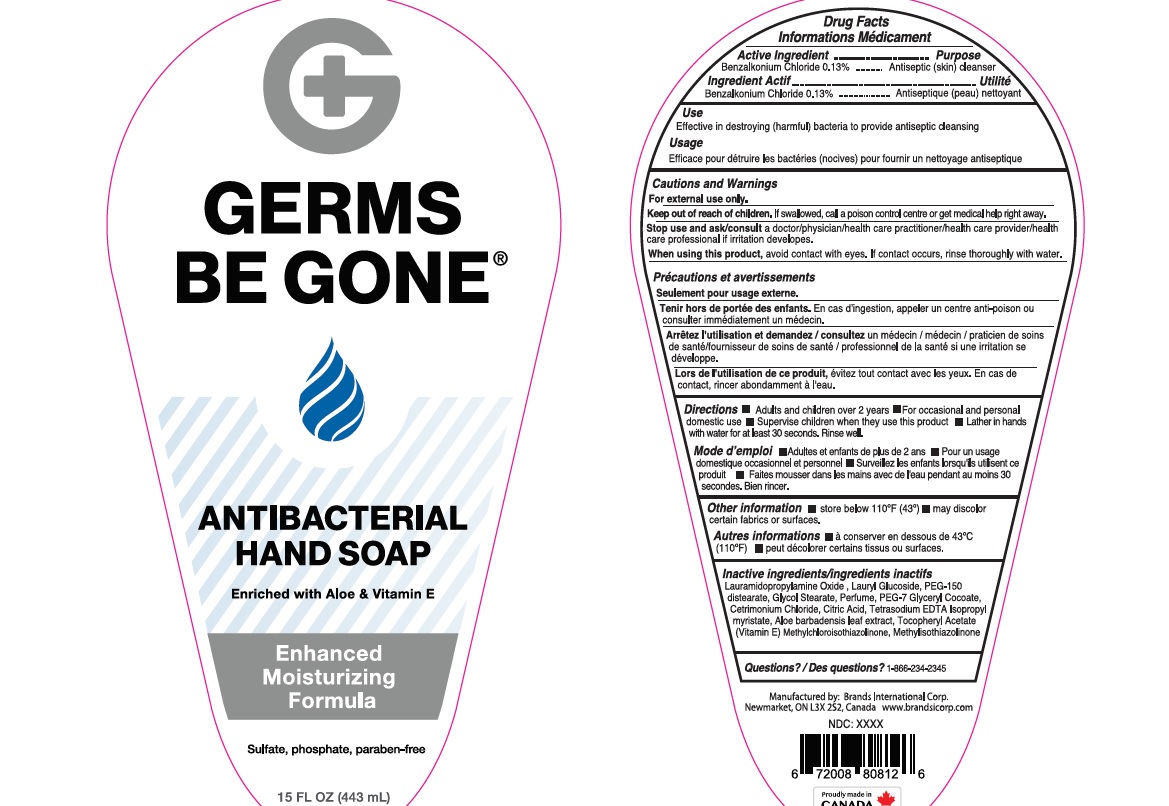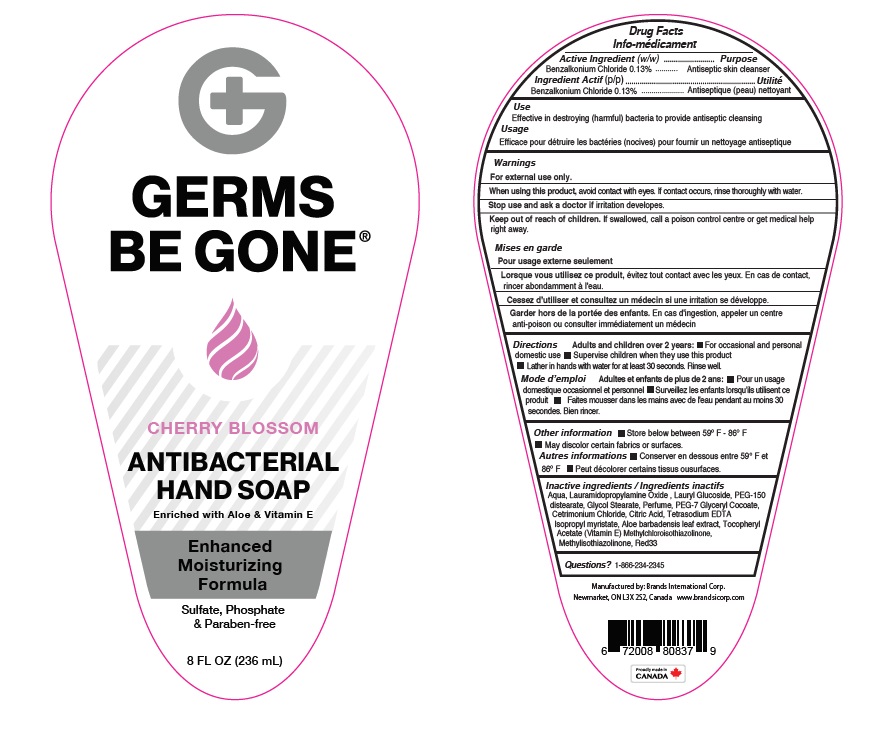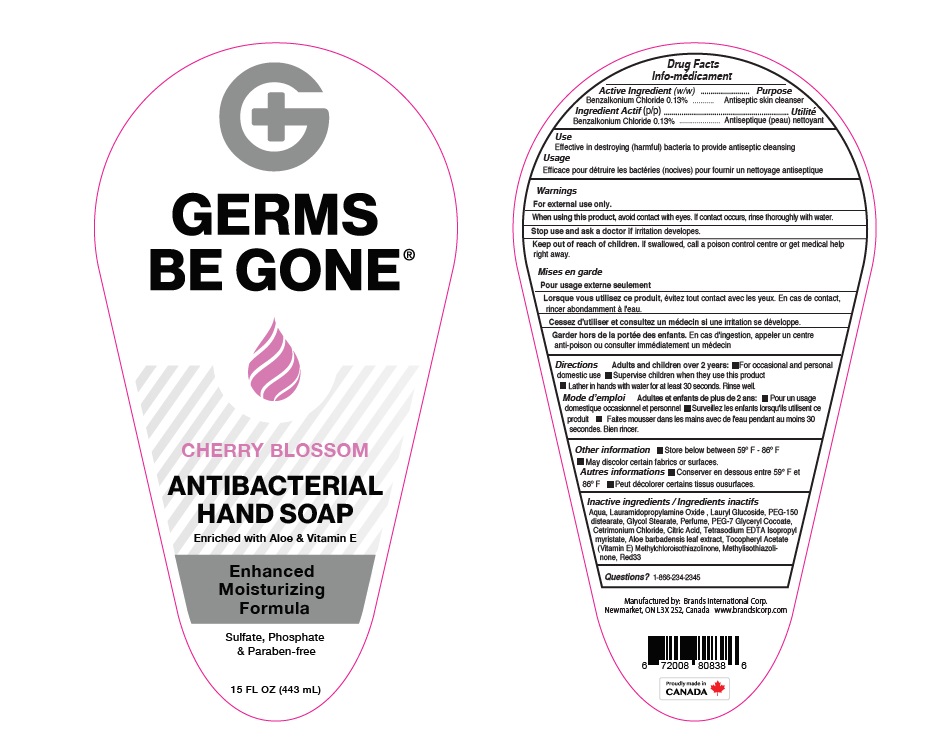 DRUG LABEL: Antibacterial Moisturizing
NDC: 50157-514 | Form: LIQUID
Manufacturer: Brands International Corporation
Category: otc | Type: HUMAN OTC DRUG LABEL
Date: 20210127

ACTIVE INGREDIENTS: BENZALKONIUM CHLORIDE 1.3 mg/1 mL
INACTIVE INGREDIENTS: CITRIC ACID MONOHYDRATE; WATER; CETRIMONIUM CHLORIDE; ISOPROPYL MYRISTATE; GLYCOL STEARATE; LAURAMIDOPROPYLAMINE OXIDE; PEG-7 GLYCERYL COCOATE; DITETRACYCLINE TETRASODIUM EDETATE; METHYLCHLOROISOTHIAZOLINONE; METHYLISOTHIAZOLINONE; .ALPHA.-TOCOPHEROL ACETATE; ALOE VERA LEAF; PEG-150 DISTEARATE; LAURYL GLUCOSIDE; D&C RED NO. 33

Germs be Gone Antibacterial Hand Soap - Cherry Blossom

ACTIVE INGREDIENT

Benzalkonium Chloride - 0.13%

Purpose - Antiseptic Skin cleanser

INDICATIONS AND USAGE

Effective in destroying (harmful) bacteria to provide antiseptic cleansing

Warnings For external use only

Stop use and ask a doctor if irritation or redness develops

When using this product

- avoid contact with eyes.
- If contact occurs, rinse eye thoroughly with water

Keep out of reach of children :

- If swallowed get medical help or contact a Poison Control Center right away

Directions:

- For occasional and personal domestic use
- Supervise children when they use this product.
- Lather in hands with water for at least 30 seconds.
- Rinse well.

INACTIVE INGREDIENT

Lauramidopropylamine oxide, Lauryl Glucoside, PEG-150 distearate, Glycol Stearate, Perfume, PEG-7 glycerly cocoate, Cetrimonium Chloride, Citric Acid, Glycerin, Tetrasodium EDTA, Methylchloroisothiazolinone, Methylisothiazolinone, Isopropyl myristate, Tocopheryl Acetate.

Red33

OTHER SAFETY INFORMATION

- Store below 59F-86F
- May discolor certain fabrics or surfaces.